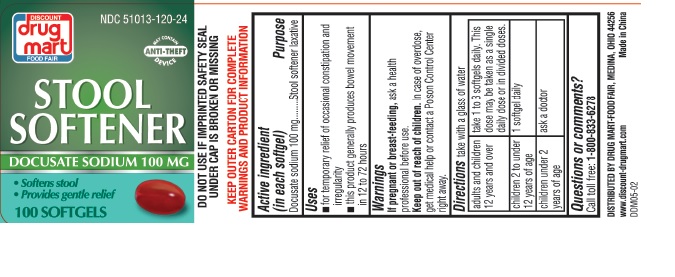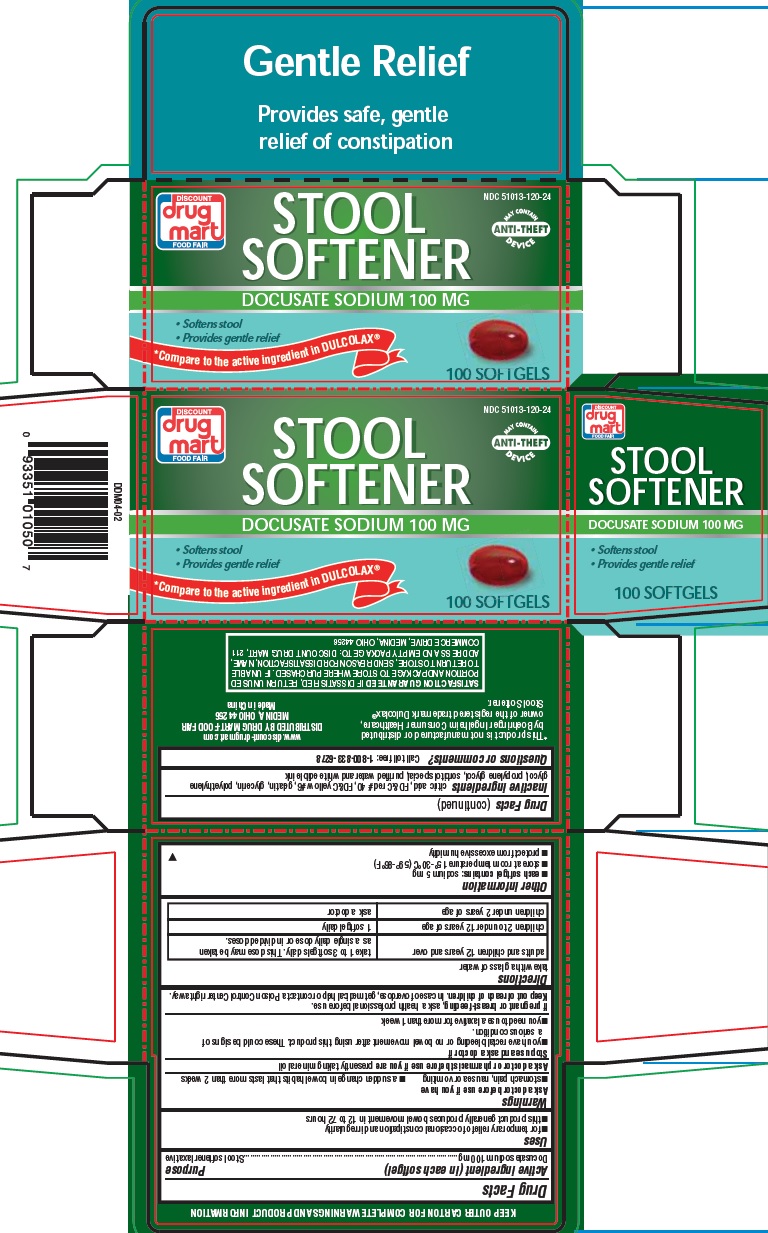 DRUG LABEL: STOOL SOFTENER
NDC: 51013-120 | Form: CAPSULE, LIQUID FILLED
Manufacturer: PuraCap Pharmaceutical LLC
Category: otc | Type: HUMAN OTC DRUG LABEL
Date: 20191211

ACTIVE INGREDIENTS: DOCUSATE SODIUM 100 mg/1 1
INACTIVE INGREDIENTS: ANHYDROUS CITRIC ACID; FD&C RED NO. 40; FD&C YELLOW NO. 6; GELATIN; GLYCERIN; POLYETHYLENE GLYCOL, UNSPECIFIED; PROPYLENE GLYCOL; WATER; SORBITOL

STOOL SOFTENER

Drug Facts

Active ingredient (in each softgel)

Docusate sodium 100 mg

Purpose

Stool softener laxative

Uses

- for temporary relief of occasional constipation and irregularity
- this product generally produces bowel movement in 12 to 72 hours

Warnings

Ask a doctor before use if you have

- stomach pain, nausea or vomiting
- a sudden change in bowel habits that lasts more than 2 weeks

Ask a doctor or pharmacist before use if you are presently taking mineral oil

Stop use and ask a doctor if

- you have rectal bleeding or no bowel movement after using this product. These could be signs of a serious condition.
- you need to use a laxative for more than 1 week

PREGNANCY OR BREAST FEEDING

If pregnant or breast-feeding, ask a health professional before use.

Keep out of reach of children.

In case of overdose, get medical help or contact a Poison Control Center right away.

Directions

take with a glass of water

adults and children 12 years and over | 1 to 3 softgels daily. This dose may be taken as a single daily dose or in divided doses.
children 2 to under 12 years of age | 1 softgel daily
children under 2 years of age | ask a doctor

Other information

- each softgel contains: sodium 5 mg
- store at room temperature 15°-30°C (59°-86°F)
- protect from excessive humidity

Inactive ingredients

citric acid, FD&C red # 40, FD&C yellow #6, gelatin, glycerin, polyethylene glycol, propylene glycol, purified water, sorbitol special and white edible ink

Questions or comments?

Call toll free: 1-800-833-6278

Principal Display Panel

STOOL SOFTENER

DOCUSATE SODIUM 100mg 100 SOFTGELS

Compare to the active ingredient in DULCOLAX®

NDC 51013-120-24